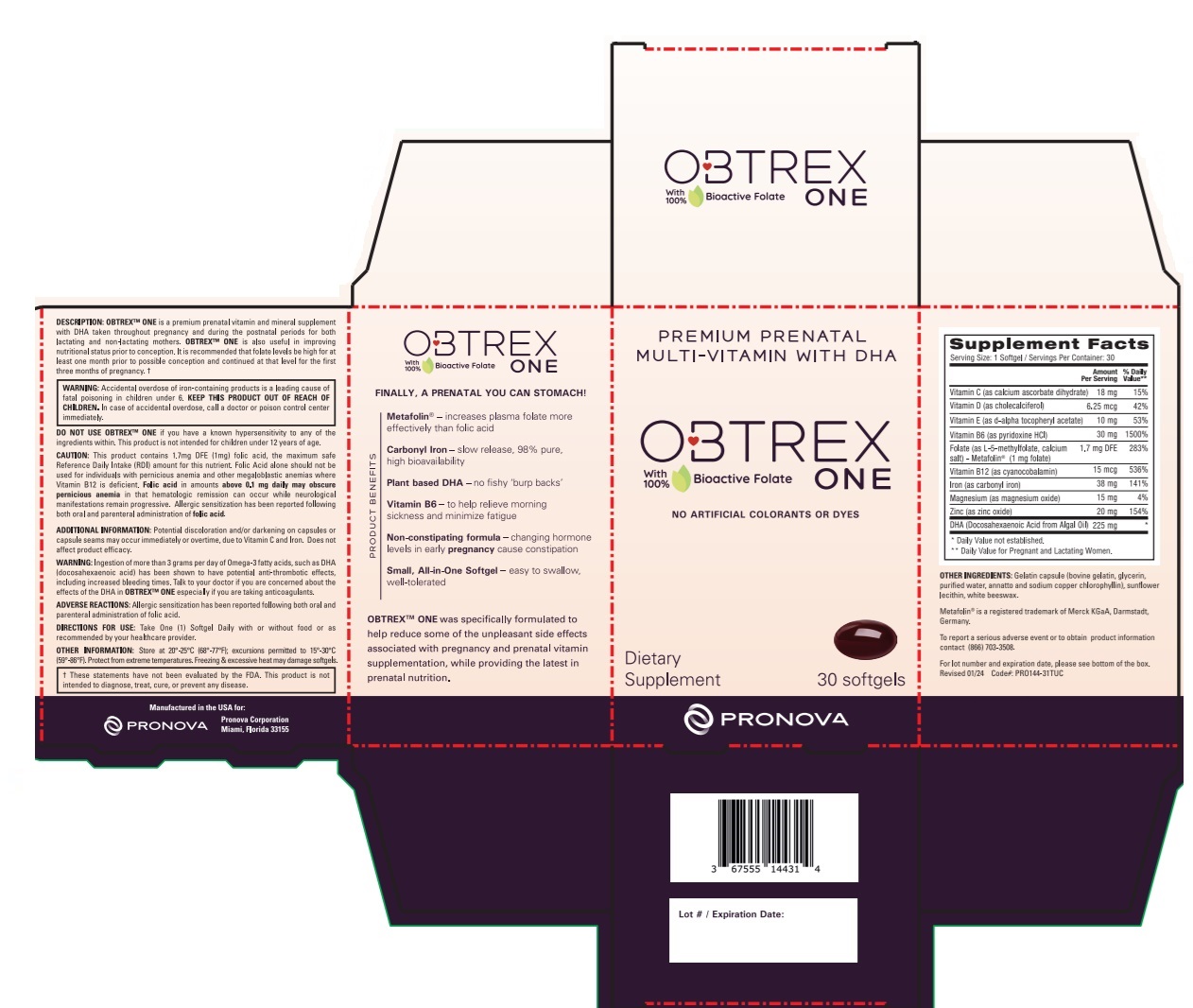 DRUG LABEL: OBTREX ONE
NDC: 67555-144 | Form: CAPSULE, GELATIN COATED
Manufacturer: Pronova Corporation
Category: other | Type: DIETARY SUPPLEMENT
Date: 20240605

ACTIVE INGREDIENTS: CALCIUM ASCORBATE 18 mg/1 1; CHOLECALCIFEROL 6.25 ug/1 1; .ALPHA.-TOCOPHEROL ACETATE, D- 10 mg/1 1; PYRIDOXINE HYDROCHLORIDE 30 mg/1 1; LEVOMEFOLATE CALCIUM 1 mg/1 1; CYANOCOBALAMIN 15 ug/1 1; IRON 38 mg/1 1; MAGNESIUM OXIDE 15 mg/1 1; ZINC OXIDE 20 mg/1 1; DOCONEXENT 225 mg/1 1
INACTIVE INGREDIENTS: GELATIN TYPE B BOVINE (230 BLOOM); GLYCERIN; WATER; ANNATTO; SODIUM COPPER CHLOROPHYLLIN; LECITHIN, SUNFLOWER; WHITE WAX

OBTREX ONE

STATEMENT OF IDENTITY

Supplement Facts
Serving Size: 1 Softgel / Servings Per Container: 30
 | Amount; Per Serving | % Daily; Value**
Vitamin C (as calcium ascorbate dihydrate) | 18 mg | 15%
Vitamin D (as cholecalciferol) | 6.25 mcg | 42%
Vitamin E (as d-alpha tocopheryl acetate) | 10 mg | 53%
Vitamin B6 (as pyridoxine HCl) | 30 mg | 1500%
Folate (as L-5-methylfolate, calcium salt) - Metafolin® (1mg folate) | 1.7 mg DFE | 283%
Vitamin B12 (as cyanocobalamin) | 15 mcg | 536%
Iron (as carbonyl iron) | 38 mg | 141%
Magnesium (as magnesium oxide) | 15 mg | 4%
Zinc (as zinc oxide) | 20 mg | 154%
DHA (Docosahexaenoic Acid from Algal Oil) | 225 mg | *
* Daily Value not established.
** Daily Value for Pregnant and Lactating Women.

OTHER INGREDIENTS: Gelatin capsule (bovine gelatin, glycerin, purified water, annatto, and sodium copper chlorophyllin), sunflower lecithin, white beeswax.

Metafolin® is a registered trademark of Merck KGaA, Darmstadt Germany.

To report a serious adverse event or to obtain product information contact (866) 703-3508.

For lot number and expiration date, please see bottom of the box.
Revised 01/2024 Code#: PRO144-31TUC

DESCRIPTION: OBTREX™ ONE is a premium prenatal vitamin and mineral supplement with DHA taken throughout pregnancy and during the postnatal periods for both lactating and non-lactating mothers. OBTREX™ ONE is also useful in improving nutritional status prior to conception. It is recommended that folate levels be high for at least one month prior to possible conception and continued at that level for the first three months of pregnancy. †

WARNINGS

WARNING: Accidental overdose of iron-containing products is a leading cause of fatal poisoning in children under 6. KEEP THIS PRODUCT OUT OF REACH OF CHILDREN. In case of accidental overdose, call a doctor or poison control center immediately.

DO NOT USE OBTREX™ ONE if you have a known hypersensitivity to any of the ingredients within. This product is not intended for children under 12 years of age.

WARNING: Ingestion of more than 3 grams per day of Omega-3 fatty acids, such as DHA (docosahexaenoic acid) has been shown to have potential anti-thrombotic effects, including increased bleeding times. Talk to your doctor if you are concerned about the effects of the DHA in OBTREX™ ONE especially if you are taking anticoagulants.

CAUTION:

This product contains 1.7mg DFE (1mg) folic acid, the maximum safe Reference Daily Intake (RDI) amount for this nutrient. Folic Acid alone should not be used for individuals with pernicious anemia and other megaloblastic anemias where Vitamin B12 is deficient. Folic acid in amounts above 0.1 mg daily may obscure pernicious anemia in that hematologic remission can occur while neurological manifestations remain progressive. Allergic sensitization has been reported following both oral and parenteral administration of folic acid.

ADDITIONAL INFORMATION: Potential discoloration and/or darkening on capsules or capsule seams may occur immediately or overtime, due to the Vitamin C and Iron. Does not affect product efficacy.

ADVERSE REACTIONS: Allergic sensitization has been reported following both oral and parenteral administration of folic acid.

DIRECTIONS FOR USE:

Take One (1) Softgel Daily with or without food or as recommended by your healthcare provider.

OTHER INFORMATION:

Store at 20°-25°C (68°-77°F); excursions permitted to 15°-30°C (59°-86°F). Protect from extreme temperatures. Freezing & excessive heat may damage softgels.

† These statements have not been evaluated by the FDA. This product is not intended to diagnose, treat, cure, or prevent any disease.

HEALTH CLAIM

Dietary Supplement

PREMIUM PRENATAL MULTI-VITAMIN WITH DHA

with 100% Bioactive Folate

NO ARTIFICIAL COLORANTS OR DYES

FINALLY, A PRENATAL YOU CAN STOMACH!

PRODUCT BENEFITS

Metafolin® - increases plasma folate more effectively than folic acid

Carbonyl Iron – slow release, 98% pure, high bioavailability

Plant based DHA – no fishy ‘burp backs’

Vitamin B6 – to help relieve morning sickness and minimize fatigue

Non-constipating formula – changing hormone levels in early pregnancy cause constipation

Small, All-in-One Softgel — easy to swallow, well-tolerated

OBTREX™ ONE was specifically formulated to help reduce some of the unpleasant side effects associated with pregnancy and prenatal vitamin supplementation, while providing the latest in prenatal nutrition.

Manufactured in the USA for:
Pronova Corporation
Miami, Florida 33155